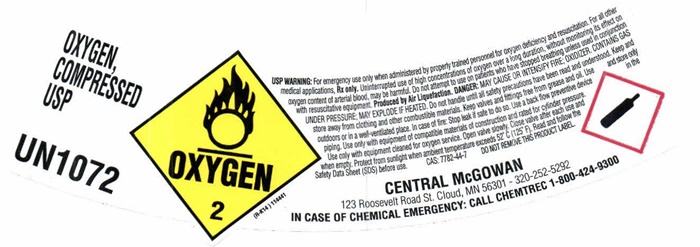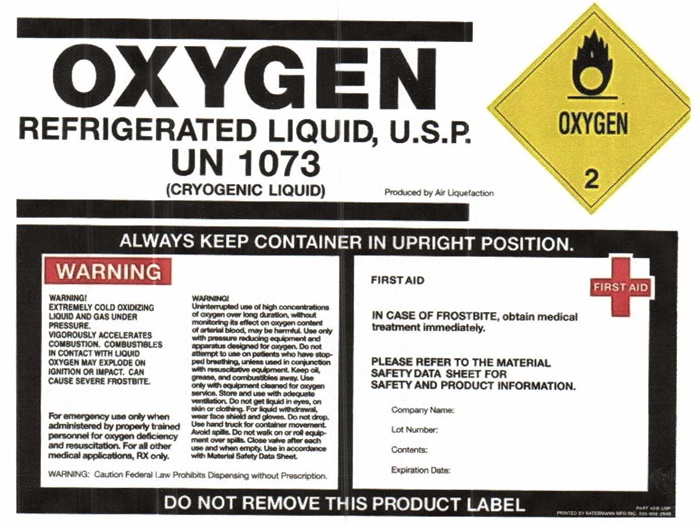 DRUG LABEL: OXYGEN
NDC: 10221-001 | Form: GAS
Manufacturer: Central-McGowan, Inc.
Category: prescription | Type: HUMAN PRESCRIPTION DRUG LABEL
Date: 20241104

ACTIVE INGREDIENTS: Oxygen 992 mL/1 L

OXYGEN - 001

PACKAGE LABEL

OXYGEN, COMPRESSED USP

UN1072 OXYGEN 2 (R-K14)

USP WARNING: For emergency use only when administered by properly trained personnel for oxygen deficiency and resuscitation. For all other medical applications, Rx only. Uninterrupted use of high concentrations of oxygen over a long duration, without monitoring its effect on oxygen content of arterial blood, may be harmful. Do not attempt to use on patients who have stopped breathing, unless used in conjunction with resuscitative equipment. Produced by Air Liquefaction. DANGER:MAY CAUSE OR INTENSIFY FIRE; OXIDIZER. CONTAINS GAS UNDER PRESSURE; MAY EXPLODE IF HEATED. Do not handle until all safety precautions have been read and understood. Keep and store away from clothing and other combustible materials. Keep valves and fittings free from grease and oil. Use and store only outdoors or in a well-ventilated place. In case of fire: Stop leak if safe to do so.Use a back flow preventive device in the piping. Use only with equipment of compatible materials of construction and rated for cylinder pressure. Use only with equipment cleaned for oxygen service. Open valve slowly. Close valve after each use and when empty. Protect from sunlight when ambient temperature exceeds 52°C (125°F). Read and follow the Safety Data Sheet (SDS) before use. CAS: 7782-44-7 DO NOT REMOVE THIS PRODUCT LABEL.

CENTRAL McGOWAN

123 Roosevelt Road St. Cloud, MN 56301 - 320-252-5292

IN CASE OF CHEMICAL EMERGENCY: CALL CHEMTREC 1-800-424-9300

PACKAGE LABEL

OXYGEN, REFRIGERATED LIQUID U.S.P.

UN1073

(CRYOGENIC LIQUID)

Produced by Air Liquefaction

OXYGEN 2

ALWAYS KEEP CONTAINER IN UPRIGHT POSITION.

WARNING

WARNING! EXTREMELY COLD OXIDIZING LIQUID AND GAS UNDER PRESSURE. VIGOROUSLY ACCELERATES COMBUSTION. COMBUSTIBLES IN CONTACT WITH LIQUID OXYGEN MAY EXPLODE ON IGNITION OR IMPACT. CAN CAUSE SEVERE FROSTBITE.

For emergency use only when administered by properly trained personnel for oxygen deficiency and resuscitation. For all other medical applications, RX only.

WARNING!

Uninterrupted use of high concentrations of oxygen over a long duration, without monitoring its effect on oxygen content of arterial blood, may be harmful. Use only with pressure reducing equipment and apparatus designed for oxygen. Do not attempt to use on patients who have stopped breathing, unless used in conjunction with resuscitative equipment. Keep oil, grease, and combustibles away. Use only with equipment cleaned for oxygen service. Store and use with adequate ventialtion. Do not get liquid in eyes, on skin, or clothing. For liquid withdrawal, wear face shield and gloves. Do not drop. Use hand truck for container movement. Avoid spills. Do not walk on or roll equipment over spills. Close valve after each use and when empty. Use in accordance with the Material Safety Data Sheet (MSDS).

WARNING: Caution Federal Law Prohibits Dispensing without Prescription.

FIRST AID

IN CASE OF FROSTBITE, obtain medical treatment immediately.

PLEASE REFER TO THE MATERIAL SAFETY DATA SHEET FOR SAFETY AND PRODUCT INFORMATION.

Company Name:

Lot Number:

Contents:

Expiration Date:

DO NOT REMOVE THIS PRODUCT LABEL